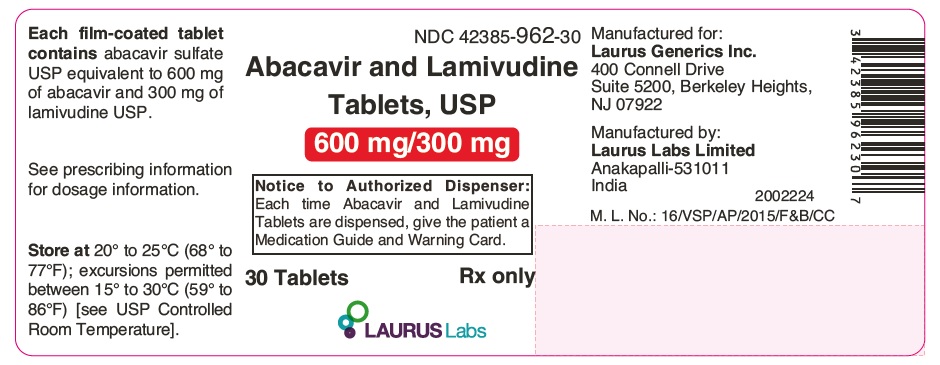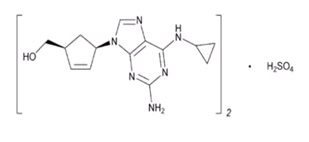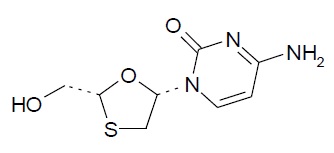 DRUG LABEL: Abacavir and Lamivudine
NDC: 42385-962 | Form: TABLET, FILM COATED
Manufacturer: Laurus Labs Limited
Category: prescription | Type: Human Prescription Drug Label
Date: 20260112

ACTIVE INGREDIENTS: ABACAVIR SULFATE 600 mg/1 1; LAMIVUDINE 300 mg/1 1
INACTIVE INGREDIENTS: MAGNESIUM STEARATE; MICROCRYSTALLINE CELLULOSE; SODIUM STARCH GLYCOLATE TYPE A POTATO; FD&C YELLOW NO. 6; HYPROMELLOSE 2910 (3 MPA.S); HYPROMELLOSE 2910 (6 MPA.S); POLYETHYLENE GLYCOL 400; POLYSORBATE 80; TITANIUM DIOXIDE

HIGHLIGHTS OF PRESCRIBING INFORMATION

These highlights do not include all the information needed to use ABACAVIR AND LAMIVUDINE TABLETS safely and effectively. See full prescribing information for ABACAVIR AND LAMIVUDINE TABLETS.
ABACAVIR and LAMIVUDINE tablets, for oral use
Initial U.S. Approval: 2004

RECENT MAJOR CHANGES

Dosage and Administration, Not Recommended Due to

Lack of Dosage Adjustment (2.4) 12/2021

WARNING: HYPERSENSITIVITY REACTIONS and EXACERBATIONS OF HEPATITIS B

See full prescribing information for complete boxed warning.

Hypersensitivity Reactions
● Serious and sometimes fatal hypersensitivity reactions have occurred with abacavir-containing products. (5.1)

● Hypersensitivity to abacavir is a multi-organ clinical syndrome. (5.1)

● Patients who carry the HLA-B*5701 allele are at a higher risk of experiencing a hypersensitivity reaction to abacavir. (5.1)

● Abacavir and lamivudine is contraindicated in patients with a prior hypersensitivity reaction to abacavir and in HLA-B*5701-positive patients. (4)

● Discontinue abacavir and lamivudine as soon as a hypersensitivity reaction is suspected. Regardless of HLA-B*5701 status, permanently discontinue abacavir and lamivudine if hypersensitivity cannot be ruled out, even when other diagnoses are possible. (5.1)

● Following a hypersensitivity reaction to abacavir and lamivudine, NEVER restart abacavir and lamivudine or any other abacavir-containing product. (5.1)
Exacerbations of Hepatitis B
● Severe acute exacerbations of hepatitis B have been reported in patients who are co-infected with hepatitis B virus (HBV) and human immunodeficiency virus (HIV-1) and have discontinued lamivudine, a component of abacavir and lamivudine. Monitor hepatic function closely in these patients and, if appropriate, initiate anti-hepatitis B treatment. (5.2)

1 INDICATIONS AND USAGE

Abacavir and lamivudine tablets, are combination of abacavir and lamivudine, both nucleoside analogue HIV-1 reverse transcriptase inhibitors, is indicated in combination with other antiretroviral agents for the treatment of HIV-1 infection. (1)

2 DOSAGE AND ADMINISTRATION

- Before initiating abacavir and lamivudine tablets, screen for the HLA-B*5701 allele because abacavir and lamivudine tablets contain abacavir. (2.1)
- Adults: One tablet orally once daily. (2.2)
- Pediatric patients weighing at least 25 kg: One tablet daily. (2.3)
- Because abacavir and lamivudine tablet is a fixed-dose tablet and cannot be dose adjusted, abacavir and lamivudine tablets are not recommended in patients with creatinine clearance less than 30 mL per minute or patients with hepatic impairment. (2.4, 4)

3 DOSAGE FORMS AND STRENGTHS

Tablets: 600 mg of abacavir and 300 mg of lamivudine. (3)

4 CONTRAINDICATIONS

- Presence of HLA-B*5701 allele. (4)
- Prior hypersensitivity reaction to abacavir or lamivudine. (4)
- Moderate or severe hepatic impairment. (4, 8.7)

5 WARNINGS AND PRECAUTIONS

- Lactic acidosis and severe hepatomegaly with steatosis, including fatal cases, have been reported with the use of nucleoside analogues. (5.3)
- Immune reconstitution syndrome has been reported in patients treated with combination antiretroviral therapy. (5.4)

6 ADVERSE REACTIONS

The most commonly reported adverse reactions of at least moderate intensity (incidence greater than 5%) in an adult HIV-1 clinical trial were drug hypersensitivity, insomnia, depression/depressed mood, headache/migraine, fatigue/malaise, dizziness/vertigo, nausea, and diarrhea. (6.1)
To report SUSPECTED ADVERSE REACTIONS, contact Laurus Generics Inc. at 1-833-3-LAURUS (1-833-352-8787) or FDA at 1-800-FDA-1088 or www.fda.gov/medwatch.

7 DRUG INTERACTIONS

- Methadone: An increased methadone dose may be required in a small number of patients. (7.1)
- Sorbitol: Coadministration of lamivudine and sorbitol may decrease lamivudine concentrations; when possible, avoid chronic coadministration. (7.2)
- Riociguat: The riociguat dose may need to be reduced. (7.3)

8 USE IN SPECIFIC POPULATIONS

- Lactation: Women infected with HIV should be instructed not to breastfeed due to potential for HIV transmission. (8.2)

FULL PRESCRIBING INFORMATION

WARNING: HYPERSENSITIVITY REACTIONS and EXACERBATIONS OF HEPATITIS B

Hypersensitivity Reactions
Serious and sometimes fatal hypersensitivity reactions, with multiple organ involvement, have occurred with abacavir, a component of abacavir and lamivudine. Patients who carry the HLA-B*5701 allele are at a higher risk of a hypersensitivity reaction to abacavir; although, hypersensitivity reactions have occurred in patients who do not carry the HLA-B*5701 allele [see Warnings and Precautions (5.1)].
Abacavir and lamivudine is contraindicated in patients with a prior hypersensitivity reaction to abacavir and in HLA-B*5701-positive patients [see Contraindications (4), Warnings and Precautions (5.1)]. All patients should be screened for the HLA-B*5701 allele prior to initiating therapy with abacavir and lamivudine or reinitiation of therapy with abacavir and lamivudine, unless patients have a previously documented HLA-B*5701 allele assessment. Discontinue abacavir and lamivudine immediately if a hypersensitivity reaction is suspected, regardless of HLA-B*5701 status and even when other diagnoses are possible [see Contraindications (4), Warnings and Precautions (5.1)].
Following a hypersensitivity reaction to abacavir and lamivudine, NEVER restart abacavir and lamivudine or any other abacavir-containing product because more severe symptoms, including death, can occur within hours. Similar severe reactions have also occurred rarely following the reintroduction of abacavir-containing products in patients who have no history of abacavir hypersensitivity [see Warnings and Precautions (5.1)].
Exacerbations of Hepatitis B

Severe acute exacerbations of hepatitis B have been reported in patients who are co-infected with hepatitis B virus (HBV) and human immunodeficiency virus (HIV-1) and have discontinued lamivudine, which is a component of abacavir and lamivudine. Hepatic function should be monitored closely with both clinical and laboratory follow-up for at least several months in patients who discontinue abacavir and lamivudine and are co-infected with HIV-1 and HBV. If appropriate, initiation of anti-hepatitis B therapy may be warranted [see Warnings and Precautions (5.2)].

1 INDICATIONS AND USAGE

Abacavir and lamivudine tablets, in combination with other antiretroviral agents, are indicated for the treatment of human immunodeficiency virus type 1 (HIV-1) infection.

2 DOSAGE AND ADMINISTRATION

2.1 Screening for HLA-B*5701 Allele Prior to Starting Abacavir and Lamivudine Tablets

Screen for the HLA-B*5701 allele prior to initiating therapy with abacavir and lamivudine tablets [see Boxed Warning, Warnings and Precautions (5.1)].

2.2 Recommended Dosage for Adult Patients

The recommended dosage of abacavir and lamivudine tablets for adults is one tablet taken orally once daily, in combination with other antiretroviral agents, with or without food.

2.3 Recommended Dosage for Pediatric Patients

The recommended oral dose of abacavir and lamivudine tablets for pediatric patients weighing at least 25 kg is one tablet daily in combination with other antiretroviral agents [see Clinical Studies (14.2)]. Before prescribing abacavir and lamivudine tablets, pediatric patients should be assessed for the ability to swallow tablets.

2.4 Not Recommended Due to Lack of Dosage Adjustment

Because abacavir and lamivudine tablet is a fixed-dose tablet and cannot be dose adjusted, abacavir and lamivudine tablets are not recommended for:

- patients with creatinine clearance less than 30 mL per minute [see Use in Specific Populations (8.6)].
- patients with mild hepatic impairment. Abacavir and lamivudine tablets are contraindicated in patients with moderate or severe hepatic impairment [see Contraindications (4), Use in Specific Populations (8.7)].

Use of EPIVIR (lamivudine) oral solution or tablets and ZIAGEN (abacavir) oral solution may be considered.

3 DOSAGE FORMS AND STRENGTHS

Abacavir and lamivudine tablets, USP contain 600 mg of abacavir as abacavir sulfate USP and 300 mg of lamivudine USP. The tablets are orange colored, capsule-shaped, biconvex film-coated tablets, debossed with “LT” on one side and plain on other side.

4 CONTRAINDICATIONS

Abacavir and lamivudine tablets are contraindicated in patients:

- who have the HLA-B*5701 allele [see Warnings and Precautions (5.1)].
- with prior hypersensitivity reaction to abacavir [see Warnings and Precautions (5.1)] or lamivudine.
- with moderate or severe hepatic impairment [see Use in Specific Populations (8.7)].

5 WARNINGS AND PRECAUTIONS

5.1 Hypersensitivity Reactions

Serious and sometimes fatal hypersensitivity reactions have occurred with abacavir, a component of abacavir and lamivudine. These hypersensitivity reactions have included multi-organ failure and anaphylaxis and typically occurred within the first 6 weeks of treatment with abacavir (median time to onset was 9 days); although abacavir hypersensitivity reactions have occurred any time during treatment [see Adverse Reactions (6.1)]. Patients who carry the HLA-B*5701 allele are at a higher risk of abacavir hypersensitivity reactions; although, patients who do not carry the HLA-B*5701 allele have developed hypersensitivity reactions. Hypersensitivity to abacavir was reported in approximately 206 (8%) of 2,670 patients in 9 clinical trials with abacavir-containing products where HLA-B*5701 screening was not performed. The incidence of suspected abacavir hypersensitivity reactions in clinical trials was 1% when subjects carrying the HLA-B*5701 allele were excluded. In any patient treated with abacavir, the clinical diagnosis of hypersensitivity reaction must remain the basis of clinical decision making.
Due to the potential for severe, serious, and possibly fatal hypersensitivity reactions with abacavir:

- All patients should be screened for the HLA-B*5701 allele prior to initiating therapy with abacavir and lamivudine or reinitiation of therapy with abacavir and lamivudine, unless patients have a previously documented HLA-B*5701 allele assessment.
- Abacavir and lamivudine is contraindicated in patients with a prior hypersensitivity reaction to abacavir and in HLA-B*5701-positive patients.
- Before starting abacavir and lamivudine, review medical history for prior exposure to any abacavir containing product. NEVER restart abacavir and lamivudine or any other abacavir-containing product following a hypersensitivity reaction to abacavir, regardless of HLA-B*5701 status.
- To reduce the risk of a life-threatening hypersensitivity reaction, regardless of HLA-B*5701 status, discontinue abacavir and lamivudine immediately if a hypersensitivity reaction is suspected, even when other diagnoses are possible (e.g., acute onset respiratory diseases such as pneumonia, bronchitis, pharyngitis, or influenza; gastroenteritis; or reactions to other medications).
- If a hypersensitivity reaction cannot be ruled out, do not restart abacavir and lamivudine or any other abacavir-containing products because more severe symptoms, which may include life-threatening hypotension and death, can occur within hours.
- If a hypersensitivity reaction is ruled out, patients may restart abacavir and lamivudine. Rarely, patients who have stopped abacavir for reasons other than symptoms of hypersensitivity have also experienced life-threatening reactions within hours of reinitiating abacavir therapy. Therefore, reintroduction of abacavir and lamivudine or any other abacavir-containing product is recommended only if medical care can be readily accessed.
- A Medication Guide and Warning Card that provide information about recognition of hypersensitivity reactions should be dispensed with each new prescription and refill.

5.2 Patients with Hepatitis B Virus Co-infection

Posttreatment Exacerbations of Hepatitis
Clinical and laboratory evidence of exacerbations of hepatitis have occurred after discontinuation of lamivudine. See full prescribing information for EPIVIR (lamivudine). Patients should be closely monitored with both clinical and laboratory follow-up for at least several months after stopping treatment.
Emergence of Lamivudine-Resistant HBV
Safety and efficacy of lamivudine have not been established for treatment of chronic hepatitis B in subjects dually infected with HIV-1 and HBV. Emergence of hepatitis B virus variants associated with resistance to lamivudine has been reported in HIV-1-infected subjects who have received lamivudine-containing antiretroviral regimens in the presence of concurrent infection with hepatitis B virus. See full prescribing information for EPIVIR (lamivudine).

5.3 Lactic Acidosis and Severe Hepatomegaly with Steatosis

Lactic acidosis and severe hepatomegaly with steatosis, including fatal cases, have been reported with the use of nucleoside analogues, including abacavir and lamivudine (components of abacavir and lamivudine). A majority of these cases have been in women. Female sex and obesity may be risk factors for the development of lactic acidosis and severe hepatomegaly with steatosis in patients treated with antiretroviral nucleoside analogues. See full prescribing information for ZIAGEN (abacavir) and EPIVIR (lamivudine). Treatment with abacavir and lamivudine should be suspended in any patient who develops clinical or laboratory findings suggestive of lactic acidosis or pronounced hepatotoxicity, which may include hepatomegaly and steatosis even in the absence of marked transaminase elevations.

5.4 Immune Reconstitution Syndrome

Immune reconstitution syndrome has been reported in patients treated with combination antiretroviral therapy, including abacavir and lamivudine. During the initial phase of combination antiretroviral treatment, patients whose immune systems respond may develop an inflammatory response to indolent or residual opportunistic infections (such as Mycobacterium avium infection, cytomegalovirus, Pneumocystis jirovecii pneumonia [PCP], or tuberculosis), which may necessitate further evaluation and treatment.
Autoimmune disorders (such as Graves’ disease, polymyositis, and Guillain-Barré syndrome) have also been reported to occur in the setting of immune reconstitution; however, the time to onset is more variable, and can occur many months after initiation of treatment.

5.5 Myocardial Infarction

Several prospective, observational, epidemiological studies have reported an association with the use of abacavir and the risk of myocardial infarction (MI). Meta-analyses of randomized, controlled clinical trials have observed no excess risk of MI in abacavir-treated subjects as compared with control subjects. To date, there is no established biological mechanism to explain the potential increase in risk. In totality, the available data from the observational studies and from controlled clinical trials show inconsistency; therefore, evidence for a causal relationship between abacavir treatment and the risk of MI is inconclusive.
As a precaution, the underlying risk of coronary heart disease should be considered when prescribing antiretroviral therapies, including abacavir, and action taken to minimize all modifiable risk factors (e.g., hypertension, hyperlipidemia, diabetes mellitus, smoking).

6 ADVERSE REACTIONS

The following adverse reactions are discussed in other sections of the labeling:

- Serious and sometimes fatal hypersensitivity reactions [see Boxed Warning, Warnings and Precautions (5.1)].
- Exacerbations of hepatitis B [see Boxed Warning, Warnings and Precautions (5.2)].
- Lactic acidosis and severe hepatomegaly with steatosis [see Warnings and Precautions (5.3)].
- Immune reconstitution syndrome [see Warnings and Precautions (5.4)].
- Myocardial infarction [see Warnings and Precautions (5.5)].

6.1 Clinical Trials Experience in Adult Subjects

Because clinical trials are conducted under widely varying conditions, adverse reaction rates observed in the clinical trials of a drug cannot be directly compared with rates in the clinical trials of another drug and may not reflect the rates observed in clinical practice.
Serious and Fatal Abacavir-Associated Hypersensitivity Reactions
In clinical trials, serious and sometimes fatal hypersensitivity reactions have occurred with abacavir, a component of abacavir and lamivudine [see Boxed Warning, Warnings and Precautions (5.1)]. These reactions have been characterized by 2 or more of the following signs or symptoms: (1) fever; (2) rash; (3) gastrointestinal symptoms (including nausea, vomiting, diarrhea, or abdominal pain); (4) constitutional symptoms (including generalized malaise, fatigue, or achiness); (5) respiratory symptoms (including dyspnea, cough, or pharyngitis). Almost all abacavir hypersensitivity reactions include fever and/or rash as part of the syndrome.
Other signs and symptoms have included lethargy, headache, myalgia, edema, arthralgia, and paresthesia. Anaphylaxis, liver failure, renal failure, hypotension, adult respiratory distress syndrome, respiratory failure, myolysis, and death have occurred in association with these hypersensitivity reactions. Physical findings have included lymphadenopathy, mucous membrane lesions (conjunctivitis and mouth ulcerations), and maculopapular or urticarial rash (although some patients had other types of rashes and others did not have a rash). There were reports of erythema multiforme. Laboratory abnormalities included elevated liver chemistries, elevated creatine phosphokinase, elevated creatinine, and lymphopenia and abnormal chest x-ray findings (predominantly infiltrates, which were localized).
Additional Adverse Reactions with Use of Abacavir and Lamivudine
Therapy-Naive Adults: Treatment-emergent clinical adverse reactions (rated by the investigator as moderate or severe) with greater than or equal to 5% frequency during therapy with ZIAGEN 600 mg once daily or ZIAGEN 300 mg twice daily, both in combination with lamivudine 300 mg once daily and efavirenz 600 mg once daily, are listed in Table 1.

Table 1. Treatment-Emergent (All Causality) Adverse Reactions of at Least Moderate Intensity (Grades 2 to 4, Greater than or Equal to 5% Frequency) in Therapy-Naive Adults (CNA30021) through 48 Weeks of Treatment
Adverse Event | ZIAGEN 600 mg q.d. plus EPIVIR plus Efavirenz (n = 384) | ZIAGEN 300 mg b.i.d. plus EPIVIR plus Efavirenz (n = 386)
Drug hypersensitivitya,b | 9% | 7%
Insomnia | 7% | 9%
Depression/Depressed mood | 7% | 7%
Headache/Migraine | 7% | 6%
Fatigue/Malaise | 6% | 8%
Dizziness/Vertigo | 6% | 6%
Nausea | 5% | 6%
Diarrheaa | 5% | 6%
Rash | 5% | 5%
Pyrexia | 5% | 3%
Abdominal pain/gastritis | 4% | 5%
Abnormal dreams | 4% | 5%
Anxiety | 3% | 5%
a Subjects receiving ZIAGEN 600 mg once daily, experienced a significantly higher incidence of severe drug hypersensitivity reactions and severe diarrhea compared with subjects who received ZIAGEN 300 mg twice daily. Five percent (5%) of subjects receiving ZIAGEN 600 mg once daily had severe drug hypersensitivity reactions compared with 2% of subjects receiving ZIAGEN 300 mg twice daily. Two percent (2%) of subjects receiving ZIAGEN 600 mg once daily had severe diarrhea while none of the subjects receiving ZIAGEN 300 mg twice daily had this event.
b CNA30024 was a multi-center, double-blind, controlled trial in which 649 HIV-1-infected, therapy-naive adults were randomized and received either ZIAGEN (300 mg twice daily), EPIVIR (150 mg twice daily), and efavirenz (600 mg once daily); or zidovudine (300 mg twice daily), EPIVIR (150 mg twice daily), and efavirenz (600 mg once daily). CNA30024 used double-blind ascertainment of suspected hypersensitivity reactions. During the blinded portion of the trial, suspected hypersensitivity to abacavir was reported by investigators in 9% of 324 subjects in the abacavir group and 3% of 325 subjects in the zidovudine group.

Laboratory Abnormalities: Laboratory abnormalities observed in clinical trials of ZIAGEN were anemia, neutropenia, liver function test abnormalities, and elevations of CPK, blood glucose, and triglycerides. Additional laboratory abnormalities observed in clinical trials of EPIVIR were thrombocytopenia and elevated levels of bilirubin, amylase, and lipase.
The frequencies of treatment-emergent laboratory abnormalities were comparable between treatment groups in CNA30021.
Other Adverse Events: In addition to adverse reactions listed above, other adverse events observed in the expanded access program for abacavir were pancreatitis and increased GGT.

6.2 Clinical Trials Experience in Pediatric Subjects

The safety of once-daily compared with twice-daily dosing of abacavir and lamivudine, administered as either single products or as abacavir and lamivudine, was assessed in the ARROW trial (n = 336). Primary safety assessment in the ARROW (COL105677) trial was based on Grade 3 and Grade 4 adverse events. The frequency of Grade 3 and 4 adverse events was similar among subjects randomized to once-daily dosing compared with subjects randomized to twice-daily dosing. One event of Grade 4 hepatitis in the once-daily cohort was considered as uncertain causality by the investigator and all other Grade 3 or 4 adverse events were considered not related by the investigator. No additional safety issues were identified in pediatric subjects receiving abacavir and lamivudine once-daily compared with historical data in adults [see Adverse Reactions (6.1)].

6.3 Postmarketing Experience

The following adverse reactions have been identified during postmarketing use. Because these reactions are reported voluntarily from a population of unknown size, it is not always possible to reliably estimate their frequency or establish a causal relationship to drug exposure.
Abacavir
Cardiovascular: Myocardial infarction.
Skin: Suspected Stevens-Johnson syndrome (SJS) and toxic epidermal necrolysis (TEN) have been reported in patients receiving abacavir primarily in combination with medications known to be associated with SJS and TEN, respectively. Because of the overlap of clinical signs and symptoms between hypersensitivity to abacavir and SJS and TEN, and the possibility of multiple drug sensitivities in some patients, abacavir should be discontinued and not restarted in such cases. There have also been reports of erythema multiforme with abacavir use [see Adverse Reactions (6.1)].
Abacavir and Lamivudine
Body as a Whole: Redistribution/accumulation of body fat.
Digestive: Stomatitis.
Endocrine and Metabolic: Hyperglycemia.
General: Weakness.
Hemic and Lymphatic: Aplastic anemia, anemia (including pure red cell aplasia and severe anemias progressing on therapy), lymphadenopathy, splenomegaly.
Hepatic: Lactic acidosis and hepatic steatosis [see Warnings and Precautions (5.3)], posttreatment exacerbations of hepatitis B [see Warnings and Precautions (5.2)].
Hypersensitivity: Sensitization reactions (including anaphylaxis), urticaria.
Musculoskeletal: Muscle weakness, creatinine phosphokinase (CPK) elevation, rhabdomyolysis.
Nervous: Paresthesia, peripheral neuropathy, seizures.
Respiratory: Abnormal breath sounds/wheezing.
Skin: Alopecia, erythema multiforme, Stevens-Johnson syndrome.

7 DRUG INTERACTIONS

7.1 Methadone

In a trial of 11 HIV-1-infected subjects receiving methadone-maintenance therapy with 600 mg of ZIAGEN twice daily (twice the currently recommended dose), oral methadone clearance increased [see Clinical Pharmacology (12.3)]. This alteration will not result in a methadone dose modification in the majority of patients; however, an increased methadone dose may be required in a small number of patients.

7.2 Sorbitol

Coadministration of single doses of lamivudine and sorbitol resulted in a sorbitol dose-dependent reduction in lamivudine exposures. When possible, avoid use of sorbitol-containing medicines with lamivudine-containing medicines [see Clinical Pharmacology (12.3)].

7.3 Riociguat

Coadministration with fixed-dose abacavir/dolutegravir/lamivudine resulted in increased riociguat exposure, which may increase the risk of riociguat adverse reactions [see Clinical Pharmacology (12.3)]. The riociguat dose may need to be reduced. See full prescribing information for ADEMPAS (riociguat).

8 USE IN SPECIFIC POPULATIONS

8.1 Pregnancy

Pregnancy Exposure Registry
There is a pregnancy exposure registry that monitors pregnancy outcomes in women exposed to abacavir and lamivudine during pregnancy. Healthcare providers are encouraged to register patients by calling the Antiretroviral Pregnancy Registry (APR) at 1-800-258-4263.
Risk Summary
Available data from the APR show no difference in the overall risk of birth defects for abacavir or lamivudine compared with the background rate for birth defects of 2.7% in the Metropolitan Atlanta Congenital Defects Program (MACDP) reference population (see Data). The APR uses the MACDP as the U.S. reference population for birth defects in the general population. The MACDP evaluates women and infants from a limited geographic area and does not include outcomes for births that occurred at less than 20 weeks’ gestation. The rate of miscarriage is not reported in the APR. The estimated background rate of miscarriage in clinically recognized pregnancies in the U.S. general population is 15% to 20%. The background risk for major birth defects and miscarriage for the indicated population is unknown.
In animal reproduction studies, oral administration of abacavir to pregnant rats during organogenesis resulted in fetal malformations and other embryonic and fetal toxicities at exposures 35 times the human exposure (AUC) at the recommended clinical daily dose. However, no adverse developmental effects were observed following oral administration of abacavir to pregnant rabbits during organogenesis, at exposures approximately 9 times the human exposure (AUC) at the recommended clinical dose. Oral administration of lamivudine to pregnant rabbits during organogenesis resulted in embryolethality at systemic exposure (AUC) similar to the recommended clinical dose; however, no adverse development effects were observed with oral administration of lamivudine to pregnant rats during organogenesis at plasma concentrations (Cmax) 35 times the recommended clinical dose (see Data).
Data
Human Data: Abacavir: Based on prospective reports to the APR of exposures to abacavir during pregnancy resulting in live births (including over 1,300 exposed in the first trimester and over 1,300 exposed in the second/third trimester), there was no difference between the overall risk of birth defects for abacavir compared with the background birth defect rate of 2.7% in the U.S. reference population of the MACDP. The prevalence of defects in live births was 3.2% (95% CI: 2.3% to 4.3%) following first trimester exposure to abacavir-containing regimens and 2.9% (95% CI: 2.1% to 4.0%) following second/third trimester exposure to abacavir-containing regimens.
Abacavir has been shown to cross the placenta and concentrations in neonatal plasma at birth were essentially equal to those in maternal plasma at delivery [see Clinical Pharmacology (12.3)].
Lamivudine: Based on prospective reports to the APR of exposures to lamivudine during pregnancy resulting in live births (including over 5,300 exposed in the first trimester and over 7,400 exposed in the second/third trimester), there was no difference between the overall risk of birth defects for lamivudine compared with the background birth defect rate of 2.7% in the U.S. reference population of the MACDP. The prevalence of birth defects in live births was 3.1% (95% CI: 2.7% to 3.6%) following first trimester exposure to lamivudine-containing regimens and 2.9% (95% CI: 2.5%, 3.3%) following second/third trimester exposure to lamivudine-containing regimens.
Lamivudine pharmacokinetics were studied in pregnant women during 2 clinical trials conducted in South Africa. The trials assessed pharmacokinetics in 16 women at 36 weeks’ gestation using 150 mg lamivudine twice daily with zidovudine, 10 women at 38 weeks’ gestation using 150 mg lamivudine twice daily with zidovudine, and 10 women at 38 weeks’ gestation using lamivudine 300 mg twice daily without other antiretrovirals. These trials were not designed or powered to provide efficacy information. Lamivudine concentrations were generally similar in maternal, neonatal, and umbilical cord serum samples. In a subset of subjects, amniotic fluid specimens were collected following natural rupture of membranes and confirmed that lamivudine crosses the placenta in humans. Based on limited data at delivery, median (range) amniotic fluid concentrations of lamivudine were 3.9 (1.2 to 12.8)–fold greater compared with paired maternal serum concentration (n = 8).
Animal Data: Abacavir: Abacavir was administered orally to pregnant rats (at 100, 300, and 1,000 mg per kg per day) and rabbits (at 125, 350, or 700 mg per kg per day) during organogenesis (on Gestation Days 6 through 17 and 6 through 20, respectively). Fetal malformations (increased incidences of fetal anasarca and skeletal malformations) or developmental toxicity (decreased fetal body weight and crown-rump length) were observed in rats at doses up to 1,000 mg per kg per day, resulting in exposures approximately 35 times the human exposure (AUC) at the recommended daily dose. No developmental effects were observed in rats at 100 mg per kg per day, resulting in exposures (AUC) 3.5 times the human exposure at the recommended daily dose. In a fertility and early embryo-fetal development study conducted in rats (at 60, 160, or 500 mg per kg per day), embryonic and fetal toxicities (increased resorptions, decreased fetal body weights) or toxicities to the offspring (increased incidence of stillbirth and lower body weights) occurred at doses up to 500 mg per kg per day. No developmental effects were observed in rats at 60 mg per kg per day, resulting in exposures (AUC) approximately 4 times the human exposure at the recommended daily dose. Studies in pregnant rats showed that abacavir is transferred to the fetus through the placenta. In pregnant rabbits, no developmental toxicities and no increases in fetal malformations occurred at up to the highest dose evaluated, resulting in exposures (AUC) approximately 9 times the human exposure at the recommended dose.
Lamivudine: Lamivudine was administered orally to pregnant rats (at 90, 600, and 4,000 mg per kg per day) and rabbits (at 90, 300 and 1,000 mg per kg per day and at 15, 40, and 90 mg per kg per day) during organogenesis (on Gestation Days 7 through 16 [rat] and 8 through 20 [rabbit]). No evidence of fetal malformations due to lamivudine was observed in rats and rabbits at doses producing plasma concentrations (Cmax) approximately 35 times higher than human exposure at the recommended daily dose. Evidence of early embryolethality was seen in the rabbit at systemic exposures (AUC) similar to those observed in humans, but there was no indication of this effect in the rat at plasma concentrations (Cmax) 35 times higher than human exposure at the recommended daily dose. Studies in pregnant rats showed that lamivudine is transferred to the fetus through the placenta. In the fertility/pre-and postnatal development study in rats, lamivudine was administered orally at doses of 180, 900, and 4,000 mg per kg per day from prior to mating through postnatal Day 20). In the study, development of the offspring, including fertility and reproductive performance, were not affected by the maternal administration of lamivudine.

8.2 Lactation

Risk Summary
The Centers for Disease Control and Prevention recommends that HIV-1-infected mothers in the United States not breastfeed their infants to avoid risking postnatal transmission of HIV-1 infection. Abacavir and lamivudine are present in human milk. There is no information on the effects of abacavir and lamivudine on the breastfed infant or the effects of the drug on milk production. Because of the potential for (1) HIV-1 transmission (in HIV-negative infants), (2) developing viral resistance (in HIV-positive infants), and (3) adverse reactions in a breastfed infant similar to those seen in adults, instruct mothers not to breastfeed if they are receiving abacavir and lamivudine.

8.4 Pediatric Use

The dosing recommendations in this population are based on the safety and efficacy established in a controlled trial conducted using either the combination of EPIVIR and ZIAGEN or abacavir and lamivudine [see Dosage and Administration (2.3), Adverse Reactions (6.2), Clinical Studies (14.2)].

In pediatric patients weighing less than 25 kg, use of abacavir and lamivudine as single products is recommended to achieve appropriate dosing.

8.5 Geriatric Use

Clinical trials of abacavir and lamivudine did not include sufficient numbers of subjects aged 65 and over to determine whether they respond differently from younger subjects. In general, caution should be exercised in the administration of abacavir and lamivudine in elderly patients reflecting the greater frequency of decreased hepatic, renal, or cardiac function, and of concomitant disease or other drug therapy [see Dosage and Administration (2.4), Use in Specific Populations (8.6, 8.7)].

8.6 Patients with Impaired Renal Function

Abacavir and lamivudine is not recommended for patients with creatinine clearance less than 30 mL per min because abacavir and lamivudine is a fixed-dose combination and the dosage of the individual components cannot be adjusted. If a dose reduction of lamivudine, a component of abacavir and lamivudine, is required for patients with creatinine clearance less than 30 mL per min, then the individual components should be used [see Clinical Pharmacology (12.3)].

Patients with a creatinine clearance between 30 and 49 mL per min receiving abacavir and lamivudine may experience a 1.6- to 3.3-fold higher lamivudine exposure (AUC) than patients with a creatinine clearance ≥50 mL per min. There are no safety data from randomized, controlled trials comparing abacavir and lamivudine to the individual components in patients with a creatinine clearance between 30 and 49 mL per min who received dose-adjusted lamivudine. In the original lamivudine registrational trials in combination with zidovudine, higher lamivudine exposures were associated with higher rates of hematologic toxicities (neutropenia and anemia), although discontinuations due to neutropenia or anemia each occurred in <1% of subjects. Patients with a sustained creatinine clearance between 30 and 49 mL per min who receive abacavir and lamivudine should be monitored for hematologic toxicities. If new or worsening neutropenia or anemia develop, dose adjustment of lamivudine, per lamivudine prescribing information, is recommended. If lamivudine dose adjustment is indicated, abacavir and lamivudine should be discontinued and the individual components should be used to construct the treatment regimen.

8.7 Patients with Impaired Hepatic Function

Abacavir and lamivudine is a fixed-dose combination and the dosage of the individual components cannot be adjusted. If a dose reduction of abacavir, a component of abacavir and lamivudine, is required for patients with mild hepatic impairment (Child-Pugh Class A), then the individual components should be used [see Clinical Pharmacology (12.3)].

The safety, efficacy, and pharmacokinetic properties of abacavir have not been established in patients with moderate (Child-Pugh Class B) or severe (Child-Pugh Class C) hepatic impairment; therefore, abacavir and lamivudine is contraindicated in these patients [see Contraindications (4)].

10 OVERDOSAGE

There is no known specific treatment for overdose with abacavir and lamivudine. If overdose occurs, the patient should be monitored, and standard supportive treatment applied as required.
Abacavir: It is not known whether abacavir can be removed by peritoneal dialysis or hemodialysis.
Lamivudine: Because a negligible amount of lamivudine was removed via (4-hour) hemodialysis, continuous ambulatory peritoneal dialysis, and automated peritoneal dialysis, it is not known if continuous hemodialysis would provide clinical benefit in a lamivudine overdose event.

11 DESCRIPTION

Abacavir and Lamivudine

Abacavir and lamivudine tablets, USP contain the following 2 synthetic nucleoside analogues: abacavir (ZIAGEN, also a component of TRIZIVIR) and lamivudine (also known as EPIVIR or 3TC) with inhibitory activity against HIV-1.

Abacavir and lamivudine tablets, USP are for oral administration. Each orange colored, capsule-shaped, biconvex film coated tablet contains the active ingredients 600 mg of abacavir as abacavir sulfate USP and 300 mg of lamivudine USP, and the inactive ingredients magnesium stearate, microcrystalline cellulose, and sodium starch glycolate. The tablets are coated with a film (OPADRY orange YS-1-13065-A) that is made of FD&C Yellow No.6, hypromellose, polyethylene glycol 400, polysorbate 80, and titanium dioxide.

Abacavir Sulfate, USP

The chemical name of abacavir sulfate, USP is (1S, 4R)-4-[2-amino-6-(cyclopropylamino)-9H-purin-9yl]-2-cyclopentene-1-methanol sulfate (salt) (2:1). Abacavir sulfate is the enantiomer with 1S, 4R absolute configuration on the cyclopentene ring. It has a molecular formula of (C14H18N6O)2•H2SO4and a molecular weight of 670.74 g per mol. It has the following structural formula:

Abacavir sulfate, USP is a white to almost white powder and is soluble in water.

In vivo, abacavir sulfate dissociates to its free base, abacavir. Dosages are expressed in terms of abacavir.

Lamivudine, USP

The chemical name of lamivudine, USP is (2(1H)-Pyrimidinone,4-amino-1-[2-(hydroxymethyl)-1,3-oxathiolan-5-yl]-, (2R-cis)-. Lamivudine, USP is the (-)enantiomer of a dideoxy analogue of cytidine. Lamivudine, USP has also been referred to as (-)2′,3′-dideoxy, 3′-thiacytidine. It has a molecular formula of C8H11N3O3S and a molecular weight of 229.26 g per mol. It has the following structural formula:

Lamivudine, USP is a white to almost white solid and is soluble in water, sparingly soluble in methanol, slightly soluble to practically insoluble in 96% ethanol and practically insoluble in acetone.

FDA approved dissolution test specifications differ from USP.

12 CLINICAL PHARMACOLOGY

12.1 Mechanism of Action

Abacavir and lamivudine is an antiretroviral agent with activity against HIV-1 [see Microbiology (12.4)].

12.3 Pharmacokinetics

Pharmacokinetics in Adults
In a single-dose, 3-way crossover bioavailability trial of 1 abacavir and lamivudine tablet versus 2 ZIAGEN tablets (2 x 300 mg) and 2 EPIVIR tablets (2 x 150 mg) administered simultaneously in healthy subjects (n = 25), there was no difference in the extent of absorption, as measured by the area under the plasma concentration-time curve (AUC) and maximal peak concentration (Cmax), of each component.
Abacavir: Following oral administration, abacavir is rapidly absorbed and extensively distributed. After oral administration of a single dose of 600 mg of abacavir in 20 subjects, Cmaxwas 4.26±1.19 mcg per mL (mean ± SD) and AUC∞ was 11.95 ± 2.51 mcg•hour per mL. Binding of abacavir to human plasma proteins is approximately 50% and was independent of concentration. Total blood and plasma drug-related radioactivity concentrations are identical, demonstrating that abacavir readily distributes into erythrocytes. The primary routes of elimination of abacavir are metabolism by alcohol dehydrogenase to form the 5’-carboxylic acid and glucuronyl transferase to form the 5’-glucuronide.
Lamivudine: Following oral administration, lamivudine is rapidly absorbed and extensively distributed. After multiple-dose oral administration of lamivudine 300 mg once daily for 7 days to 60 healthy subjects, steady-state Cmax(Cmax,ss) was 2.04 ± 0.54 mcg per mL (mean ± SD) and the 24-hour steady-state AUC (AUC24,ss) was 8.87 ± 1.83 mcg•hour per mL. Binding to plasma protein is low. Approximately 70% of an intravenous dose of lamivudine is recovered as unchanged drug in the urine. Metabolism of lamivudine is a minor route of elimination. In humans, the only known metabolite is the trans-sulfoxide metabolite (approximately 5% of an oral dose after 12 hours).
In humans, abacavir and lamivudine are not significantly metabolized by cytochrome P450 (CYP) enzymes.
The pharmacokinetic properties of abacavir and lamivudine in fasting subjects are summarized in Table 2.

Table 2. Pharmacokinetic Parametersa for Abacavir and Lamivudine in Adults
Parameter | Abacavir |  | Lamivudine
Oral bioavailability (%) | 86 ± 25 | n = 6 | 86 ± 16 | n = 12
Apparent volume of distribution (L/kg) | 0.86 ± 0.15 | n = 6 | 1.3 ± 0.4 | n = 20
Systemic clearance (L/h/kg) | 0.80 ± 0.24 | n = 6 | 0.33 ± 0.06 | n = 20
Renal clearance (L/h/kg) | 0.007 ± 0.008 | n = 6 | 0.22 ± 0.06 | n = 20
Elimination half-life (h) | 1.45 ± 0.32 | n = 20 | 13 to 19b
a Data presented as mean ± standard deviation except where noted.
b Approximate range.

Effect of Food on Absorption of Abacavir And Lamivudine
Abacavir and lamivudine may be administered with or without food. Administration with a high-fat meal in a single-dose bioavailability trial resulted in no change in AUClast, AUC∞, and Cmaxfor lamivudine. Food did not alter the extent of systemic exposure to abacavir (AUC∞), but the rate of absorption (Cmax) was decreased approximately 24% compared with fasted conditions (n = 25). These results are similar to those from previous trials of the effect of food on abacavir and lamivudine tablets administered separately.
Specific Populations
Patients with Renal Impairment: The pharmacokinetics for the individual lamivudine component of abacavir and lamivudine has been evaluated in patients with renal impairment (see the U.S. prescribing information for the individual lamivudine component).
Patients with Hepatic Impairment: The pharmacokinetics for the individual components of abacavir and lamivudine have been evaluated in patients with varying degrees of hepatic impairment (see the U.S. prescribing information for the individual abacavir and lamivudine components).
Pregnant Women: Abacavir: Abacavir pharmacokinetics were studied in 25 pregnant women during the last trimester of pregnancy receiving abacavir 300 mg twice daily. Abacavir exposure (AUC) during pregnancy was similar to those in postpartum and in HIV-infected non-pregnant historical controls. Consistent with passive diffusion of abacavir across the placenta, abacavir concentrations in neonatal plasma cord samples at birth were essentially equal to those in maternal plasma at delivery.
Lamivudine: Lamivudine pharmacokinetics were studied in 36 pregnant women during 2 clinical trials conducted in South Africa. Lamivudine pharmacokinetics in pregnant women were similar to those seen in non-pregnant adults and in postpartum women. Lamivudine concentrations were generally similar in maternal, neonatal, and umbilical cord serum samples.
Pediatric Patients: Abacavir and Lamivudine: The pharmacokinetic data for abacavir and lamivudine following administration ofabacavir and lamivudine in pediatric subjects weighing 25 kg and above are limited. The dosing recommendations in this population are based on the safety and efficacy established in a controlled trial conducted using either the combination of EPIVIR and ZIAGEN or abacavir and lamivudine. Refer to the EPIVIR and ZIAGEN USPI for pharmacokinetic information on the individual products in pediatric patients [see Dosage and Administration (2.3), Adverse Reactions (6.2), Clinical Studies (14.2)].
Geriatric Patients: The pharmacokinetics of abacavir and lamivudine have not been studied in subjects over 65 years of age.
Male and Female Patients: There are no significant or clinically relevant gender differences in the pharmacokinetics of the individual components (abacavir or lamivudine) based on the available information that was analyzed for each of the individual components.
Racial Groups: There are no significant or clinically relevant racial differences in pharmacokinetics of the individual components (abacavir or lamivudine) based on the available information that was analyzed for each of the individual components.
Drug Interaction Studies
The drug interactions described are based on trials conducted with abacavir or lamivudine as single entities; no drug interaction trials have been conducted with abacavir and lamivudine.
Effect of Abacavir and Lamivudine on the Pharmacokinetics of Other Agents: In vitro studies have shown that abacavir has potential to inhibit CYP1A1 and limited potential to inhibit metabolism mediated by CYP3A4. Lamivudine does not inhibit or induce CYP3A4. Abacavir and lamivudine do not inhibit or induce other CYP enzymes (such as CYP2C9 or CYP2D6). Based on in vitro study results, abacavir and lamivudine at therapeutic drug exposures are not expected to affect the pharmacokinetics of drugs that are substrates of the following transporters: organic anion transporter polypeptide (OATP)1B1/3, breast cancer resistance protein (BCRP) or P-glycoprotein (P-gp), organic cation transporter (OCT)1, OCT2, OCT3 (lamivudine only), or multidrug and toxic extrusion protein (MATE)1 and MATE2-K.
Riociguat: Coadministration of a single dose of riociguat (0.5 mg) to HIV-1–infected subjects receiving fixed-dose abacavir/dolutegravir/lamivudine is reported to increase riociguat AUC(∞)compared with riociguat AUC(∞)reported in healthy subjects due to CYP1A1 inhibition by abacavir. The exact magnitude of increase in riociguat exposure has not been fully characterized based on findings from two studies [see Drug Interactions (7.3)].
Effect of Other Agents on the Pharmacokinetics of Abacavir or Lamivudine: Abacavir and lamivudine are not significantly metabolized by CYP enzymes; therefore, CYP enzyme inhibitors or inducers are not expected to affect their concentrations. In vitro, abacavir is not a substrate of OATP1B1, OATP1B3, OCT1, OCT2, OAT1, MATE1, MATE2-K, multidrug resistance-associated protein 2 (MRP2) or MRP4; therefore, drugs that modulate these transporters are not expected to affect abacavir plasma concentrations. Abacavir is a substrate of BCRP and P-gp in vitro; however, considering its absolute bioavailability (83%), modulators of these transporters are unlikely to result in a clinically relevant impact on abacavir concentrations.
Lamivudine is a substrate of MATE1, MATE2-K, and OCT2 in vitro. Trimethoprim (an inhibitor of these drug transporters) has been shown to increase lamivudine plasma concentrations. This interaction is not considered clinically significant as no dose adjustment of lamivudine is needed.
Lamivudine is a substrate of P-gp and BCRP; however, considering its absolute bioavailability (87%), it is unlikely that these transporters play a significant role in the absorption of lamivudine. Therefore, coadministration of drugs that are inhibitors of these efflux transporters is unlikely to affect the disposition and elimination of lamivudine.
Abacavir: Lamivudine and/or Zidovudine: Fifteen HIV-1-infected subjects were enrolled in a crossover-designed drug interaction trial evaluating single doses of abacavir (600 mg), lamivudine (150 mg), and zidovudine (300 mg) alone or in combination. Analysis showed no clinically relevant changes in the pharmacokinetics of abacavir with the addition of lamivudine or zidovudine or the combination of lamivudine and zidovudine. Lamivudine exposure (AUC decreased 15%) and zidovudine exposure (AUC increased 10%) did not show clinically relevant changes with concurrent abacavir.
Lamivudine: Zidovudine: No clinically significant alterations in lamivudine or zidovudine pharmacokinetics were observed in 12 asymptomatic HIV-1-infected adult subjects given a single dose of zidovudine (200 mg) in combination with multiple doses of lamivudine (300 mg every 12 h).
Other Interactions
Ethanol: Abacavir has no effect on the pharmacokinetic properties of ethanol. Ethanol decreases the elimination of abacavir causing an increase in overall exposure.
Interferon Alfa: There was no significant pharmacokinetic interaction between lamivudine and interferon alfa in a trial of 19 healthy male subjects.
Methadone: In a trial of 11 HIV-1-infected subjects receiving methadone-maintenance therapy (40 mg and 90 mg daily), with 600 mg of ZIAGEN twice daily (twice the currently recommended dose), oral methadone clearance increased 22% (90% CI: 6% to 42%) [see Drug Interactions (7)]. The addition of methadone has no clinically significant effect on the pharmacokinetic properties of abacavir.
Ribavirin: In vitro data indicate ribavirin reduces phosphorylation of lamivudine, stavudine, and zidovudine. However, no pharmacokinetic (e.g., plasma concentrations or intracellular triphosphorylated active metabolite concentrations) or pharmacodynamic (e.g., loss of HIV-1/HCV virologic suppression) interaction was observed when ribavirin and lamivudine (n = 18), stavudine (n = 10), or zidovudine (n = 6) were coadministered as part of a multi-drug regimen to HIV-1/HCV co-infected subjects.
Sorbitol (Excipient): Lamivudine and sorbitol solutions were coadministered to 16 healthy adult subjects in an open-label, randomized-sequence, 4-period, crossover trial. Each subject received a single 300-mg dose of lamivudine oral solution alone or coadministered with a single dose of 3.2 grams, 10.2 grams, or 13.4 grams of sorbitol in solution. Coadministration of lamivudine with sorbitol resulted in dose-dependent decreases of 20%, 39%, and 44% in the AUC(0 to 24); 14%, 32%, and 36% in the AUC(∞); and 28%, 52%, and 55% in the Cmax; of lamivudine, respectively.

The effects of other coadministered drugs on abacavir or lamivudine are provided in Table 3.

Table 3. Effect of Coadministered Drugs on Abacavir or Lamivudine
Coadministered Drug and Dose | Drug and Dose | n | Concentrations of Abacavir or Lamivudine |  | Concentration of Coadministered Drug
Coadministered Drug and Dose | Drug and Dose | n | AUC | Variability | Concentration of Coadministered Drug
Ethanol 0.7 g/kg | Abacavir Single 600 mg | 24 | ↑41% | 90% CI: 35% to 48% | ↔a
Nelfinavir 750 mg every 8 h x 7 to 10 days | Lamivudine Single 150 mg | 11 | ↑10% | 95% CI: 1% to 20% | ↔
Trimethoprim 160 mg/ Sulfamethoxazole 800 mg daily x 5 days | Lamivudine Single 300 mg | 14 | ↑43% | 90% CI: 32% to 55% | ↔
↑= Increase; ↔= No significant change; AUC = Area under the concentration versus time curve; CI = Confidence interval.
a The drug-drug interaction was only evaluated in males.

12.4 Microbiology

Mechanism of Action
Abacavir: Abacavir is a carbocyclic synthetic nucleoside analogue. Abacavir is converted by cellular enzymes to the active metabolite, carbovir triphosphate (CBV-TP), an analogue of deoxyguanosine-5’-triphosphate (dGTP). CBV-TP inhibits the activity of HIV-1 reverse transcriptase (RT) both by competing with the natural substrate dGTP and by its incorporation into viral DNA.
Lamivudine: Lamivudine is a synthetic nucleoside analogue. Intracellularly lamivudine is phosphorylated to its active 5’-triphosphate metabolite, lamivudine triphosphate (3TC-TP). The principal mode of action of 3TC-TP is inhibition of RT via DNA chain termination after incorporation of the nucleotide analogue.
Antiviral Activity
Abacavir: The antiviral activity of abacavir against HIV-1 was assessed in a number of cell lines including primary monocytes/macrophages and peripheral blood mononuclear cells (PBMCs). EC50values ranged from 3,700 to 5,800 nM (1 nM = 0.28 ng per mL) and 70 to 1,000 nM against HIV-1IIIBand HIV-1BaL, respectively, and the mean EC50value was 260 ± 180 nM against 8 clinical isolates. The median EC50values of abacavir were 344 nM (range: 14.8 to 676 nM), 16.9 nM (range: 5.9 to 27.9 nM), 8.1 nM (range: 1.5 to 16.7 nM), 356 nM (range: 35.7 to 396 nM), 105 nM (range: 28.1 to 168 nM), 47.6 nM (range: 5.2 to 200 nM), 51.4 nM (range: 7.1 to 177 nM), and 282 nM (range: 22.4 to 598 nM) against HIV-1 clades A to G and group O viruses (n = 3 except n = 2 for clade B), respectively. The EC50values against HIV-2 isolates (n = 4) ranged from 24 to 490 nM.
Lamivudine: The antiviral activity of lamivudine against HIV-1 was assessed in a number of cell lines including monocytes and PBMCs using standard susceptibility assays. EC50values were in the range of 3 to 15,000 nM (1 nM = 0.23 ng per mL). The median EC50values of lamivudine were 60 nM (range: 20 to 70 nM), 35 nM (range: 30 to 40 nM), 30 nM (range: 20 to 90 nM), 20 nM (range: 3 to 40 nM), 30 nM (range: 1 to 60 nM), 30 nM (range: 20 to 70 nM), 30 nM (range: 3 to 70 nM), and 30 nM (range: 20 to 90 nM) against HIV-1 clades A to G and group O viruses (n = 3 except n = 2 for clade B), respectively. The EC50values against HIV-2 isolates (n = 4) ranged from 3 to 120 nM in PBMCs. Ribavirin (50,000 nM) used in the treatment of chronic HCV infection decreased the anti-HIV-1 activity of lamivudine by 3.5-fold in MT-4 cells.
The combination of abacavir and lamivudine has demonstrated antiviral activity in cell culture against non-subtype B isolates and HIV-2 isolates with equivalent antiviral activity as for subtype B isolates. Neither abacavir, nor lamivudine, were antagonistic to all tested anti-HIV agents. See full prescribing information for ZIAGEN (abacavir) and EPIVIR (lamivudine). Ribavirin, used in the treatment of HCV infection, decreased the anti-HIV-1 potency of abacavir/lamivudine reproducibly by 2- to 6-fold in cell culture.
Resistance
HIV-1 isolates with reduced susceptibility to the combination of abacavir and lamivudine have been selected in cell culture with amino acid substitutions K65R, L74V, Y115F, and M184V/I emerging in HIV-1 RT. M184V or I substitutions resulted in high-level resistance to lamivudine and an approximately 2-fold decrease in susceptibility to abacavir. Substitutions K65R, L74M, or Y115F with M184V or I conferred a 7- to 8-fold reduction in abacavir susceptibility, and combinations of three substitutions were required to confer more than an 8-fold reduction in susceptibility.
Cross-Resistance
Cross-resistance has been observed among nucleoside reverse transcriptase inhibitors (NRTIs). The combination of abacavir/lamivudine has demonstrated decreased susceptibility to viruses with a K65R substitution with or without an M184V/I substitution, viruses with L74V plus the M184V/I substitution, and viruses with thymidine analog mutation substitutions (TAMs: M41L, D67N, K70R, L210W, T215Y/F, K219E/R/H/Q/N) plus M184V. An increasing number of TAMs is associated with a progressive reduction in abacavir susceptibility.

13 NONCLINICAL TOXICOLOGY

13.1 Carcinogenesis, Mutagenesis, Impairment of Fertility

Carcinogenicity
Abacavir: Abacavir was administered orally at 3 dosage levels to separate groups of mice and rats in 2-year carcinogenicity studies. Results showed an increase in the incidence of malignant and non-malignant tumors. Malignant tumors occurred in the preputial gland of males and the clitoral gland of females of both species, and in the liver of female rats. In addition, non-malignant tumors also occurred in the liver and thyroid gland of female rats. These observations were made at systemic exposures in the range of 6 to 32 times the human exposure at the recommended dose of 600 mg.
Lamivudine: Long-term carcinogenicity studies with lamivudine in mice and rats showed no evidence of carcinogenic potential at exposures up to 10 times (mice) and 58 times (rats) the human exposures at the recommended dose of 300 mg.
Mutagenicity
Abacavir: Abacavir induced chromosomal aberrations both in the presence and absence of metabolic activation in an in vitro cytogenetic study in human lymphocytes. Abacavir was mutagenic in the absence of metabolic activation, although it was not mutagenic in the presence of metabolic activation in an L5178Y mouse lymphoma assay. Abacavir was clastogenic in males and not clastogenic in females in an in vivo mouse bone marrow micronucleus assay. Abacavir was not mutagenic in bacterial mutagenicity assays in the presence and absence of metabolic activation.
Lamivudine: Lamivudine was mutagenic in an L5178Y mouse lymphoma assay and clastogenic in a cytogenetic assay using cultured human lymphocytes. Lamivudine was not mutagenic in a microbial mutagenicity assay, in an in vitro cell transformation assay, in a rat micronucleus test, in a rat bone marrow cytogenetic assay, and in an assay for unscheduled DNA synthesis in rat liver.
Impairment of Fertility
Abacavir: Abacavir did not affect male or female fertility in rats at a dose associated with exposures (AUC) approximately 3.3 times (male) or 4.1 times (female) those in humans at the clinically recommended dose.
Lamivudine: Lamivudine did not affect male or female fertility in rats at doses up to 4,000 mg per kg per day, associated with concentrations approximately 42 times (male) or 63 times (female) higher than the concentrations (Cmax) in humans at the dose of 300 mg.

13.2 Animal Toxicology and/or Pharmacology

Myocardial degeneration was found in mice and rats following administration of abacavir for 2 years. The systemic exposures were equivalent to 7 to 24 times the expected systemic exposure in humans at a dose of 600 mg. The clinical relevance of this finding has not been determined.

14 CLINICAL STUDIES

14.1 Adults

One abacavir and lamivudine tablet given once daily is an alternative regimen to EPIVIR tablets 300 mg once daily plus ZIAGEN tablets 2 x 300 mg once daily as a component of antiretroviral therapy.
The following trial was conducted with the individual components of abacavir and lamivudine.
Therapy-Naive Adults
CNA30021 was an international, multicenter, double-blind, controlled trial in which 770 HIV-1-infected, therapy-naive adults were randomized and received either ZIAGEN 600 mg once daily or ZIAGEN 300 mg twice daily, both in combination with EPIVIR 300 mg once daily and efavirenz 600 mg once daily. The double-blind treatment duration was at least 48 weeks. Trial participants had a mean age of 37 years; were male (81%), white (54%), black (27%), and American Hispanic (15%). The median baseline CD4+ cell count was 262 cells per mm^3 (range: 21 to 918 cells per mm^3) and the median baseline plasma HIV-1 RNA was 4.89 log10copies per mL (range: 2.60 to 6.99 log10copies per mL).
The outcomes of randomized treatment are provided in Table 4.

Table 4. Outcomes of Randomized Treatment through Week 48 (CNA30021)
Outcome | ZIAGEN 600 mg q.d. plus EPIVIR plus Efavirenz (n = 384) | ZIAGEN 300 mg b.i.d. plus EPIVIR plus Efavirenz (n = 386)
Respondera | 64% (71%) | 65% (72%)
Virologic failureb | 11% (5%) | 11% (5%)
Discontinued due to adverse reactions | 13% | 11%
Discontinued due to other reasonsc | 11% | 13%
a Subjects achieved and maintained confirmed HIV-1 RNA less than 50 copies per mL (less than 400 copies per mL) through Week 48 (Roche AMPLICOR Ultrasensitive HIV-1 MONITOR standard test version 1.0).
b Includes viral rebound, failure to achieve confirmed less than 50 copies per mL (less than 400 copies per mL) by Week 48, and insufficient viral load response.
c Includes consent withdrawn, lost to follow-up, protocol violations, clinical progression, and other.

After 48 weeks of therapy, the median CD4+ cell count increases from baseline were 188 cells per mm^3 in the group receiving ZIAGEN 600 mg once daily and 200 cells per mm^3 in the group receiving ZIAGEN 300 mg twice daily. Through Week 48, 6 subjects (2%) in the group receiving ZIAGEN 600 mg once daily (4 CDC classification C events and 2 deaths) and 10 subjects (3%) in the group receiving ZIAGEN 300 mg twice daily (7 CDC classification C events and 3 deaths) experienced clinical disease progression. None of the deaths were attributed to trial medications.

14.2 Pediatric Subjects

ARROW (COL105677) was a 5-year, randomized, multicenter trial which evaluated multiple aspects of clinical management of HIV-1 infection in pediatric subjects. HIV-1–infected, treatment-naïve subjects aged 3 months to 17 years were enrolled and treated with a first-line regimen containing abacavir and lamivudine, dosed twice daily according to World Health Organization recommendations. After a minimum of 36 weeks of treatment, subjects were given the option to participate in Randomization 3 of the ARROW trial, comparing the safety and efficacy of once-daily dosing with twice-daily dosing of abacavir and lamivudine, in combination with a third antiretroviral drug, for an additional 96 weeks. Virologic suppression was not a requirement for participation at baseline for Randomization 3. At baseline for Randomization 3 (following a minimum of 36 weeks of twice-daily treatment), 75% of subjects in the twice-daily cohort were virologically suppressed, compared with 71% of subjects in the once-daily cohort.

Of the 1,206 original ARROW subjects, 669 participated in Randomization 3. Subjects randomized to receive once-daily dosing (n = 336) and who weighed at least 25 kg received abacavir 600 mg and lamivudine 300 mg, as either the single entities or as abacavir and lamivudine.

The proportions of subjects with HIV-1 RNA less than 80 copies per mL through 96 weeks are shown in Table 5. The differences between virologic responses in the two treatment arms were comparable across baseline characteristics for gender and age.

Table 5. Virologic Outcome of Randomized Treatment at Week 96a(ARROW Randomization 3)
Outcome | Abacavir plus Lamivudine Twice-Daily Dosing (n = 333) | Abacavir plus Lamivudine Once-Daily Dosing (n = 336)
HIV-1 RNA <80 copies/mLb | 70% | 67%
HIV-1 RNA ≥80 copies/mLc No virologic data | 28% | 31%
Discontinued due to adverse event or death | 1% | <1%
Discontinued study for other reasonsd | 0% | <1%
Missing data during window but on study | 1% | 1%
a Analyses were based on the last observed viral load data within the Week 96 window.
b Risk difference (95% CI) of response rate is -2.4% (-9% to 5%) at Week 96.
c Includes subjects who discontinued due to lack or loss of efficacy or for reasons other than an adverse event or death, and had a viral load value of greater than or equal to 80 copies per mL, or subjects who had a switch in background regimen that was not permitted by the protocol.
d Other includes reasons such as withdrew consent, loss to follow-up, etc. and the last available
HIV-1 RNA less than 80 copies per mL (or missing).

16 HOW SUPPLIED/STORAGE AND HANDLING

Abacavir and lamivudine tablets, USP contain 600 mg of abacavir as abacavir sulfate USP and 300 mg of lamivudine USP. The tablets are orange colored, capsule-shaped, biconvex film coated tablets, debossed with “LT” on one side and plain on other side. They are packaged as follows:
Bottles of 30 tablets NDC 42385-962-30
Bottles of 90 tablets NDC 42385-962-90
Bottles of 180 tablets NDC 42385-962-18
Store at 20° to 25°C (68° to 77°F), excursions permitted between 15° to 30°C (59° to 86°F). [see USP Controlled Room Temperature.]

17 PATIENT COUNSELING INFORMATION

Advise the patient to read the FDA-approved patient labeling (Medication Guide).
Hypersensitivity Reactions
Inform patients:

- that a Medication Guide and Warning Card summarizing the symptoms of the abacavir hypersensitivity reaction and other product information will be dispensed by the pharmacist with each new prescription and refill of abacavir and lamivudine tablets and instruct the patient to read the Medication Guide and Warning Card every time to obtain any new information that may be present about abacavir and lamivudine tablets. The complete text of the Medication Guide is reprinted at the end of this document.
- to carry the Warning Card with them.
- how to identify a hypersensitivity reaction [see Warnings and Precautions (5.1), Medication Guide].
- that if they develop symptoms consistent with a hypersensitivity reaction they should call their healthcare provider right away to determine if they should stop taking abacavir and lamivudine tablets.
- that a hypersensitivity reaction can worsen and lead to hospitalization or death if abacavir and lamivudine tablets are not immediately discontinued.
- to not restart abacavir and lamivudine tablets or any other abacavir-containing product following a hypersensitivity reaction because more severe symptoms can occur within hours and may include life-threatening hypotension and death.
- that if they have a hypersensitivity reaction, they should dispose of any unused abacavir and lamivudine tablets to avoid restarting abacavir.
- that a hypersensitivity reaction is usually reversible if it is detected promptly and abacavir and lamivudine tablets are stopped right away.
- that if they have interrupted abacavir and lamivudine tablets for reasons other than symptoms of hypersensitivity (for example, those who have an interruption in drug supply), a serious or fatal hypersensitivity reaction may occur with reintroduction of abacavir.
- to not restart abacavir and lamivudine tablets or any other abacavir-containing product without medical consultation and only if medical care can be readily accessed by the patient or others.

Patients with Hepatitis B or C Co-infection
Advise patients co-infected with HIV-1 and HBV that worsening of liver disease has occurred in some cases when treatment with lamivudine was discontinued. Advise patients to discuss any changes in regimen with their physician [see Warnings and Precautions (5.2)].
Lactic Acidosis/Hepatomegaly with Steatosis
Advise patients that lactic acidosis and severe hepatomegaly with steatosis have been reported with use of nucleoside analogues and other antiretrovirals. Advise patients to stop taking abacavir and lamivudine tablets if they develop clinical symptoms suggestive of lactic acidosis or pronounced hepatotoxicity [see Warnings and Precautions (5.3)].
Immune Reconstitution Syndrome
Advise patients to inform their healthcare provider immediately of any signs and symptoms of infection as inflammation from previous infection may occur soon after combination antiretroviral therapy, including when abacavir and lamivudine tablets are started [see Warnings and Precautions (5.4)].
Pregnancy Registry
Advise patients that there is a pregnancy exposure registry that monitors pregnancy outcomes in women exposed to abacavir and lamivudine tablets during pregnancy [see Use in Specific Populations (8.1)].
Lactation
Instruct women with HIV-1 infection not to breastfeed because HIV-1 can be passed to the baby in the breast milk [see Use in Specific Populations (8.2)].
Missed Dose
Instruct patients that if they miss a dose of abacavir and lamivudine tablets, to take it as soon as they remember. Advise patients not to double their next dose or take more than the prescribed dose [see Dosage and Administration (2)].
Availability of Medication Guide
Instruct patients to read the Medication Guide before starting abacavir and lamivudine tablets and to re-read it each time the prescription is renewed. Instruct patients to inform their physician or pharmacist if they develop any unusual symptom, or if any known symptom persists or worsens.
EPIVIR, TRIZIVIR, and ZIAGEN are trademarks owned by or licensed to the ViiV Healthcare group of companies.
The other brands listed are trademarks owned by or licensed to their respective owners and are not owned by or licensed to Laurus Labs Limited. The makers of these brands are not affiliated with and do not endorse Laurus Labs Limited or its products.

Manufactured for:
Laurus Generics Inc.
400 Connell Drive
Suite 5200
Berkeley Heights, NJ 07922
Manufactured by:
Laurus Labs Limited
Anakapalli-531011
India

MEDICATION GUIDE
Abacavir and Lamivudine
(a-BAK-a-veer and la-MI-vyoo-deen)
Tablets, USP

What is the most important information I should know about abacavir and lamivudine tablets?
Abacavir and lamivudine tablets can cause serious side effects, including:
• Serious allergic reactions (hypersensitivity reaction) that can cause death have happened with abacavir and lamivudine tablets and other abacavir-containing products. Your risk of this allergic reaction is much higher if you have a gene variation called HLA-B*5701. Your healthcare provider can determine with a blood test if you have this gene variation.
If you get a symptom from 2 or more of the following groups while taking abacavir and lamivudine tablets, call your healthcare provider right away to find out if you should stop taking abacavir and lamivudine tablets.
Symptom(s)
Group 1 Fever
Group 2 Rash
Group 3 Nausea, vomiting, diarrhea, abdominal (stomach area) pain
Group 4 Generally ill feeling, extreme tiredness, or achiness
Group 5 Shortness of breath, cough, sore throat
A list of these symptoms is on the Warning Card your pharmacist gives you. Carry this Warning Card with you at all times.
If you stop abacavir and lamivudine tablets because of an allergic reaction, never take abacavir and lamivudine tablets (abacavir and lamivudine) or any other abacavir-containing medicine (TRIUMEQ, TRIZIVIR, or ZIAGEN) again.
o If you have an allergic reaction, dispose of any unused abacavir and lamivudine tablets. Ask your pharmacist how to properly dispose of medicines.
o If you take abacavir and lamivudine tablets or any other abacavir-containing medicine again after you have had an allergic reaction, within hours you may get life-threatening symptoms that may include very low blood pressure or death.
o If you stop abacavir and lamivudine tablets for any other reason, even for a few days, and you are not allergic to abacavir and lamivudine tablets, talk with your healthcare provider before taking it again. Taking abacavir and lamivudine tablets again can cause a serious allergic or life-threatening reaction, even if you never had an allergic reaction to it before.
If your healthcare provider tells you that you can take abacavir and lamivudine tablets again, start taking them when you are around medical help or people who can call a healthcare provider if you need one.
• Worsening of hepatitis B virus (HBV) infection. If you have HBV infection and take abacavir and lamivudine tablets, your HBV may get worse (flare-up) if you stop taking abacavir and lamivudine tablets. A “flare-up” is when your HBV infection suddenly returns in a worse way than before.
o Do not run out of abacavir and lamivudine tablets. Refill your prescription or talk to your healthcare provider before your abacavir and lamivudine tablets are all gone.
o Do not stop abacavir and lamivudine tablets without first talking to your healthcare provider.
o If you stop taking abacavir and lamivudine tablets, your healthcare provider will need to check your health often and do blood tests regularly for several months to check your liver function and monitor your HBV infection. It may be necessary to give you a medicine to treat HBV. Tell your healthcare provider about any new or unusual symptoms you may have after you stop taking abacavir and lamivudine tablets.
• Resistant HBV. If you have human immunodeficiency virus-1 (HIV-1) and HBV, the HBV can change (mutate) during your treatment with abacavir and lamivudine tablets and become harder to treat (resistant).
• For more information about side effects, see “What are the possible side effects of abacavir and lamivudine tablets?”

What are abacavir and lamivudine tablets?
Abacavir and lamivudine tablets are a prescription medicine used with other HIV-1 medicines to treat HIV-1 infection.
HIV-1 is the virus that causes Acquired Immune Deficiency Syndrome (AIDS).
Abacavir and lamivudine tablets contain the prescription medicines abacavir and lamivudine.
Abacavir and lamivudine tablets should not be used in children weighing less than 55 pounds (25 kg).

Do not take abacavir and lamivudine tablets if you:
• have a certain type of gene variation called the HLA-B*5701 allele. Your healthcare provider will test you for this before prescribing treatment with abacavir and lamivudine tablets.
• are allergic to abacavir, lamivudine, or any of the ingredients in abacavir and lamivudine tablets. See the end of this Medication Guide for a complete list of ingredients in abacavir and lamivudine tablets.
• have certain liver problems.

Before you take abacavir and lamivudine tablets tell your healthcare provider about all of your medical conditions, including if you:
• have been tested and know whether or not you have a particular gene variation called HLA-B*5701.
• have or have had liver problems, including hepatitis B or C virus infection.
• have kidney problems.
• have heart problems, smoke, or have diseases that increase your risk of heart disease such as high blood pressure, high cholesterol, or diabetes.
• are pregnant or plan to become pregnant.
Pregnancy Registry. There is a pregnancy registry for women who take HIV-1 medicines during pregnancy. The purpose of this registry is to collect information about the health of you and your baby. Talk to your healthcare provider about how you can take part in this registry.
• are breastfeeding or plan to breastfeed. Do not breastfeed if you take abacavir and lamivudine tablets.
o You should not breastfeed if you have HIV-1 because of the risk of passing HIV-1 to your baby.
Tell your healthcare provider about all the medicines you take, including prescription and over-the-counter medicines, vitamins, and herbal supplements.
Some medicines interact with abacavir and lamivudine tablets. Keep a list of your medicines to show your healthcare provider and pharmacist when you get a new medicine.
• You can ask your healthcare provider or pharmacist for a list of medicines that interact with abacavir and lamivudine tablets.
• Do not start taking a new medicine without telling your healthcare provider. Your healthcare provider can tell you if it is safe to take abacavir and lamivudine tablets with other medicines.

How should I take abacavir and lamivudine tablets?
• Take abacavir and lamivudine tablets exactly as your healthcare provider tells you to take them.
• Do not change your dose or stop taking abacavir and lamivudine tablets without talking with your healthcare provider.
• If you miss a dose of abacavir and lamivudine tablets, take it as soon as you remember. Do not take 2 doses at the same time or take more than your healthcare provider tells you to take.
• Stay under the care of a healthcare provider during treatment with abacavir and lamivudine tablets.
• Abacavir and lamivudine tablets may be taken with or without food.
• Tell your healthcare provider if your child has trouble swallowing abacavir and lamivudine tablets.
• Do not run out of abacavir and lamivudine tablets. The virus in your blood may increase and the virus may become harder to treat. When your supply starts to run low, get more from your healthcare provider or pharmacy
• If you take too much abacavir and lamivudine tablets, call your healthcare provider or go to the nearest hospital emergency room right away.

What are the possible side effects of abacavir and lamivudine tablets?
• Abacavir and lamivudine tablets can cause serious side effects including:
• See “What is the most important information I should know about abacavir and lamivudine tablets?”
• Too much lactic acid in your blood (lactic acidosis). Lactic acidosis is a serious medical emergency that can cause death. Call your healthcare provider right away if you get any of the following symptoms that could be signs of lactic acidosis:
o feel very weak or tired
o unusual (not normal) muscle pain
o trouble breathing
o stomach pain with nausea and vomiting
o feel cold, especially in your arms and legs
o feel dizzy or light-headed
o have a fast or irregular heartbeat
• Severe liver problems. In some cases, severe liver problems can lead to death. Your liver may become large (hepatomegaly) and you may develop fat in your liver (steatosis). Call your healthcare provider right away if you get any of the following signs or symptoms of liver problems:
o your skin or the white part of your eyes turns yellow (jaundice)
o dark or “tea-colored” urine
o light-colored stools (bowel movements)
o loss of appetite for several days or longer
o nausea
o pain, aching, or tenderness on the right side of your stomach area
You may be more likely to get lactic acidosis or severe liver problems if you are female or very overweight (obese).
• Changes in your immune system (Immune Reconstitution Syndrome) can happen when you start taking HIV-1 medicines. Your immune system may get stronger and begin to fight infections that have been hidden in your body for a long time. Tell your healthcare provider right away if you start having new symptoms after you start taking abacavir and lamivudine tablets.
• Heart attack. Some HIV-1 medicines including abacavir and lamivudine tablets may increase your risk of heart attack.
The most common side effects of abacavir and lamivudine tablets include:
• allergic reactions
• trouble sleeping
• depression
• headache or migraine
• tiredness or weakness
• dizziness
• nausea
• diarrhea
Tell your healthcare provider if you have any side effect that bothers you or that does not go away.
These are not all the possible side effects of abacavir and lamivudine tablets. Call your doctor for medical advice about side effects. You may report side effects to FDA at 1-800-FDA-1088.

How should I store abacavir and lamivudine tablets?
• Store abacavir and lamivudine tablets at room temperature.
Keep abacavir and lamivudine tablets and all medicines out of the reach of children.

General information for safe and effective use of abacavir and lamivudine tablets.
Medicines are sometimes prescribed for purposes other than those listed in a Medication Guide. Do not use abacavir and lamivudine tablets for a condition for which it was not prescribed. Do not give abacavir and lamivudine tablets to other people, even if they have the same symptoms that you have. It may harm them. You can ask your healthcare provider or pharmacist for information about abacavir and lamivudine tablets that is written for health professionals.
For more information, call Laurus Generics Inc. at 1-833-3-LAURUS (1-833-352-8787).

What are the ingredients in abacavir and lamivudine tablets?
Active ingredients: abacavir sulfate USP and lamivudine USP
Inactive ingredients: magnesium stearate, microcrystalline cellulose, sodium starch glycolate.
Tablet film coating contains: OPADRY orange YS-1-13065-A made of FD&C Yellow No. 6, hypromellose, polyethylene glycol 400, polysorbate 80, and titanium dioxide.
This Medication Guide has been approved by the U.S. Food and Drug Administration.
TRIUMEQ, TRIZIVIR, and ZIAGEN are trademarks owned by or licensed to the ViiV Healthcare group of companies.
The other brands listed are trademarks owned by or licensed to their respective owners and are not trademarks owned by or licensed to Laurus Labs Limited. The makers of these brands are not affiliated with and do not endorse Laurus Labs Limited or its products.
Manufactured for:
Laurus Generics Inc.
400 Connell Drive
Suite 5200
Berkeley Heights, NJ 07922
Manufactured by:
Laurus Labs Limited
Anakapalli-531011
India
Revised: 9/2024

(Front of card)

WARNING CARD

Abacavir and Lamivudine Tablets

Patients taking abacavir and lamivudine tablets may have a serious allergic reaction (hypersensitivity reaction) that can cause death. If you get a symptom from 2 or more of the following groups while taking abacavir and lamivudine tablets, call your healthcare provider right away to find out if you should stop taking this medicine.

 | Symptom(s)
Group 1 | Fever
Group 2 | Rash
Group 3 | Nausea, vomiting, diarrhea, or abdominal (stomach area) pain
Group 4 | Generally ill feeling, extreme tiredness, or achiness
Group 5 | Shortness of breath, cough, or sore throat

Always carry this Warning Card with you to help recognize symptoms of this allergic reaction.

(Back of Card)

WARNING CARD

Abacavir and Lamivudine Tablets

If you must stop treatment with abacavir and lamivudine tablets because you have had an allergic reaction to abacavir, NEVER take abacavir and lamivudine tablets or another abacavir-containing medicine (ZIAGEN®, TRIUMEQ®, or TRIZIVIR®) again. If you have an allergic reaction, dispose of any unused abacavir, and lamivudine tablets. Ask your pharmacist how to properly dispose of medicines. If you take abacavir and lamivudine tablets or another abacavir-containing medicine again after you have had an allergic reaction, WITHIN HOURS you may get life-threatening symptoms that may include very low blood pressure or death.

Please read the Medication Guide for additional information on abacavir and lamivudine tablets.

The brands listed are trademarks of their respective owners and are not trademarks of Laurus Labs Limited.

Revised: 03/2022

PRINCIPAL DISPLAY PANEL - Container Label (30's count)

NDC 42385-962-30
Abacavir and Lamivudine
Tablets, USP
600 mg/300 mg
Notice to Authorized Dispenser.
Each time Abacavir and Lamivudine
Tablets are dispensed. give the
patient a Medication Guide and
Warning Card.
30 Tablets RX Only
LAURUS Labs